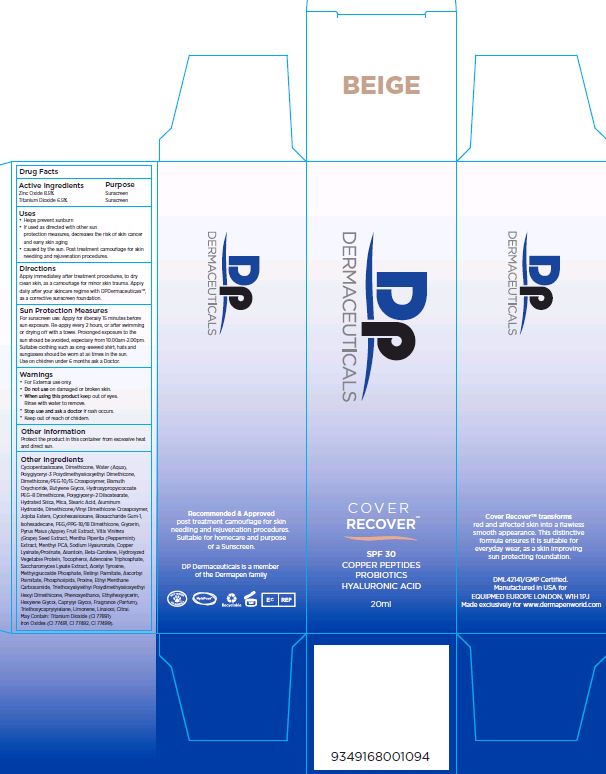 DRUG LABEL: Cover Recover SPF 30 Beige
NDC: 62742-4119 | Form: CREAM
Manufacturer: Allure Labs, Inc
Category: otc | Type: HUMAN OTC DRUG LABEL
Date: 20171205

ACTIVE INGREDIENTS: ZINC OXIDE 85.0 mg/1 mL; TITANIUM DIOXIDE 65.0 mg/1 mL
INACTIVE INGREDIENTS: CYCLOMETHICONE 5; DIMETHICONE; WATER; POLYGLYCERYL-3 POLYDIMETHYLSILOXYETHYL DIMETHICONE (4000 MPA.S); BISMUTH OXYCHLORIDE; BUTYLENE GLYCOL; HYDROXYPROPYLCOCOATE PEG-8 DIMETHICONE; POLYGLYCERYL-2 DIISOSTEARATE; HYDRATED SILICA; MICA; STEARIC ACID; ALUMINUM HYDROXIDE; DIMETHICONE/VINYL DIMETHICONE CROSSPOLYMER (SOFT PARTICLE); JOJOBA OIL, RANDOMIZED; TRIEPOXYCYCLOHEXASILANE; BIOSACCHARIDE GUM-1; ISOHEXADECANE; PEG/PPG-18/18 DIMETHICONE; GLYCERIN; APPLE; VITIS VINIFERA SEED; MENTHA PIPERITA; MENTHYL DL-PYRROLIDONECARBOXYLATE; HYALURONATE SODIUM; ALLANTOIN; .BETA.-CAROTENE; TOCOPHEROL; ADENOSINE TRIPHOSPHATE; SACCHAROMYCES LYSATE; N-ACETYLTYROSINE; VITAMIN A PALMITATE; ASCORBYL PALMITATE; EGG PHOSPHOLIPIDS; PROLINE; ETHYL MENTHANE CARBOXAMIDE; PHENOXYETHANOL; ETHYLHEXYLGLYCERIN; HEXYLENE GLYCOL; CAPRYLYL GLYCOL; TRIETHOXYCAPRYLYLSILANE; LIMONENE, (+)-; LINALOOL, (+)-; CITRAL; FERRIC OXIDE RED; FERRIC OXIDE YELLOW; FERROSOFERRIC OXIDE

Drug Facts

ACTIVE INGREDIENT

Zinc Oxide 8.5%

Titanium Dioxide 6.5%

PURPOSE

Sunscreen

INDICATIONS AND USAGE

Uses: Helps prevent sunburn.

if used as directed with other sun protection measures, decreases the rsk of skin cancer and early skin aging caused by the sun.

post treatment camouflage for skin needling and rejuvenation procedures.

DOSAGE AND ADMINISTRATION

Directions: Apply immediately after treatment procedures, to dry clean skin, as a acamouflage for minor skin trauma. Apply daily after your skincare regime with DPDermaceuticals, as a corrective sunscreen foundation.

Sun protection measures: For sunscreen use

Apply for liberally 15 minutes before sun exposure. Re-apply every 2 hours, or after swimming or drying off with a towel. Prolonged exposure to the sun should be avoided, especially from 10:00am - 2:00pm. Suitable clothing such as long-sleeved shirt, hats, and sunglasses should be worn at all times in the sun. Use on children under 6 months ask a doctor.

WARNINGS

For external use only.

do not use on damaged or broken skin.

when using this product keep out of eyes.

rinse with water to remove.

stop use and ask a doctor if rash occurs.

keep out of reach of children.

OTHER SAFETY INFORMATION

Protect the product in this container from excessive heat and direct sun.

INACTIVE INGREDIENT

Cyclopentasiloxane, Dimethicone, Water (Aqua), Polyglyceryl-3-Polydimethylsiloxyethyl Dimethicone, Dimethicone/PEG-10/15 Crosspolymer, Bismuth Oxychloride, Butylene Glycol, Hydroxypropylcocoate PE-8 Dimethicone, Polyglyceryl-2 Diisostearate, Hydrated Silica, Mica, Stearic Acid, Aluminum Hydroxide, Dimethicone/Vinyl Dimethicone Crosspolymer, Jojoba Esters, Cyclohexasiloxane, Biosaccharide Gum-1, Isohexadecane, PEG/PPG-18/18 Dimethicone, Glycerin, Pyrus Malus (Apple) Fruit Extract, Vitis Vinifera (Grape) Seed Extract, Mentha Piperita (Peppermint) Extract, Menthyl PCA, Sodium Hyaluronate, Copper Lysinate/Rolinate, Allantoin, Beta-Carotene, Hydrolyzed Vegetable Protein, Tocopherol, Adenosine Triphosphate, Saccharomyces Lysate Extract, Acetyl Tyrosine, Methylglucoside Phosphate, Retinyl Palmitate, Ascorbyl palmitate, Phospholipids, Proline, Ethyl menthane carboxamide, Triethoxysilylethyl Polydimethylsiloxyethyl HexylDimethicone, Phenoxyethanol, Ethylhexylglycerin, Hexylene Glycol, Caprylyl Glycol, Fragrance (Parfum), Triethoxycaprylysilane, Limonene, Linalool, citral, May contain:(+/-) Titanium Dioxide (CI 77891), Iron Oxides (CI 77491, CI 77492, CI 77499)

PACKAGE LABEL

DML42141/GMP Certified.

manufactured in USA for

EQUIPMED EUROPE LONDON, W1H 1PJ

Made exclusively for www.dermapenworld.com